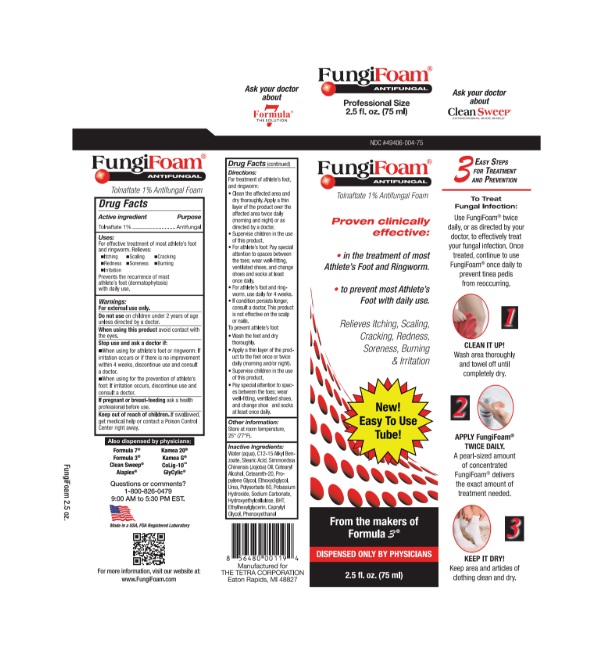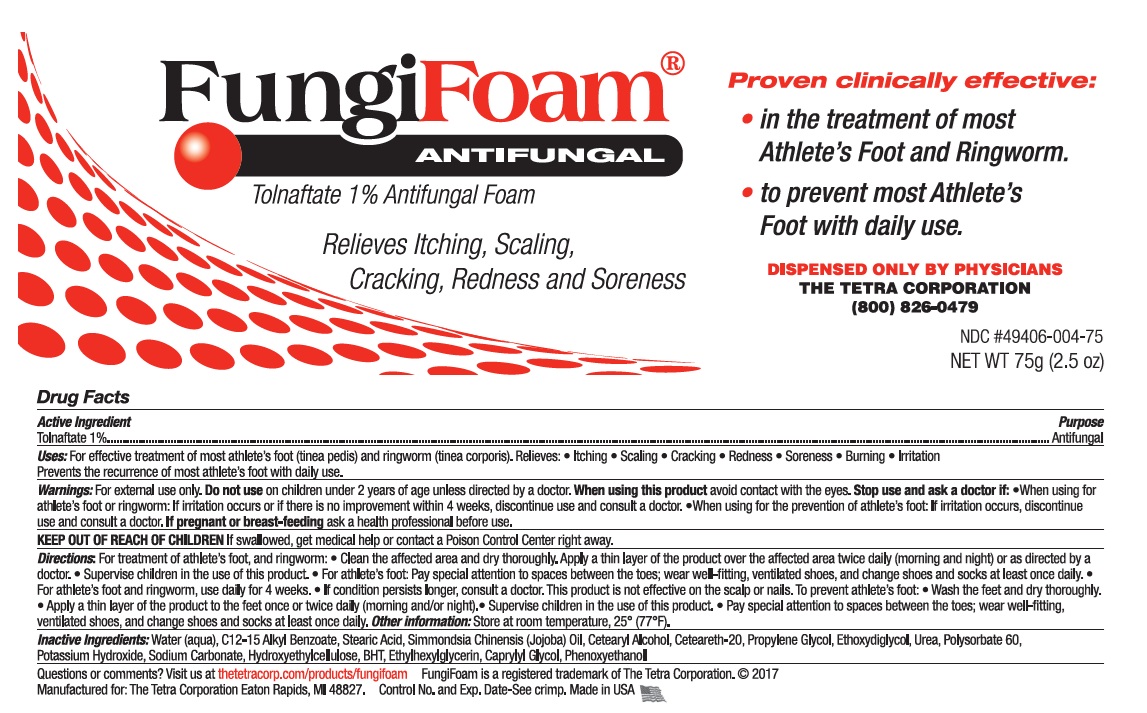 DRUG LABEL: FungiFoam
NDC: 49406-004 | Form: AEROSOL, FOAM
Manufacturer: The Tetra Corporation
Category: otc | Type: HUMAN OTC DRUG LABEL
Date: 20250818

ACTIVE INGREDIENTS: TOLNAFTATE 10 mg/1 mL
INACTIVE INGREDIENTS: BUTYLATED HYDROXYTOLUENE; ALKYL (C12-15) BENZOATE; POLYOXYL 20 CETOSTEARYL ETHER; CETOSTEARYL ALCOHOL; ETHYLHEXYLGLYCERIN; STEARIC ACID; PHENOXYETHANOL; POLYSORBATE 60; PROPYLENE GLYCOL; JOJOBA OIL; UREA; WATER; POTASSIUM HYDROXIDE; SODIUM CARBONATE; HYDROXYETHYL CELLULOSE, UNSPECIFIED; CAPRYLYL GLYCOL; DIETHYLENE GLYCOL MONOETHYL ETHER

FungiFoam ANTIFUNGAL

Active Ingredient

Tolnaftate 1%

Purpose

Antifungal

Uses:

For effective treatment of most athlete's foot (tinea pedis), and ringworm (tinea corporis).
Relieves:

- itching
- scaling
- cracking
- redness
- soreness
- burning
- irritation

Prevents the recurrence of most athlete's foot with daily use.

Warnings

For external use only.

When using this productavoid contact with the eyes.

Stop use and ask a doctor if:

- When using for treatment of athlete's foot or ringworm: If irritation occurs or if there is no improvement within 4 weeks, discontinue use and consult a doctor.
- When using for prevention of athlete's foot: If irritation occurs, discontinue use and consult a doctor.

Do not useon children under 2 years of age unless directed by a doctor.

Keep out of reach of children.

If swallowed, get medical help or contact a Poison Control Center right away.

If pregnant or breast-feeding

ask a health professional before use.

Directions:

For treatment of athlete's foot, and ring-worm:

- Clean the affected area and dry thoroughly. Apply a thin layer of the product over the affected area twice daily (morning and night) or as directed by a doctor.
- Supervise children in the use of this product
- For athlete's foot: Pay special attention to spaces between the toes; wear well-fitting, ventilated shoes, and change shoes and socks at least once daily.
- For athlete's foot and ringworm, use daily for 4 weeks.
- If condition persists longer, consult a doctor. This product is not effective on the scalp or nails.

To prevent athlete's foot:

- Wash the feet and dry thoroughly.
- Apply a thin layer of the product to the feet once or twice daily (morning and/or night)
- Supervise children in the use of this product.
- Pay special attention to spaces between the toes; wear well-fitting, ventilated shoes, and change shoes and socks at least once daily.

Other information:

Store at room temperature, 25 degrees Celsius (77 degrees Fahrenheit).

Inactive ingredients:

Water (aqua), C12-15 Alkyl Benzoate, Stearic acid, Simmondsia chinensis (jojoba) oil, Cetearyl alcohol, Ceteareth-20, Propylene glycol, Ethoxydiglycol, Urea, Polysorbate 60, Potassium hydroxide, Sodium carbonate, Hydroxyethylcellulose, BHT, Ethylhexylglycerin, Caprylyl glycol, Phenoxyethanol.